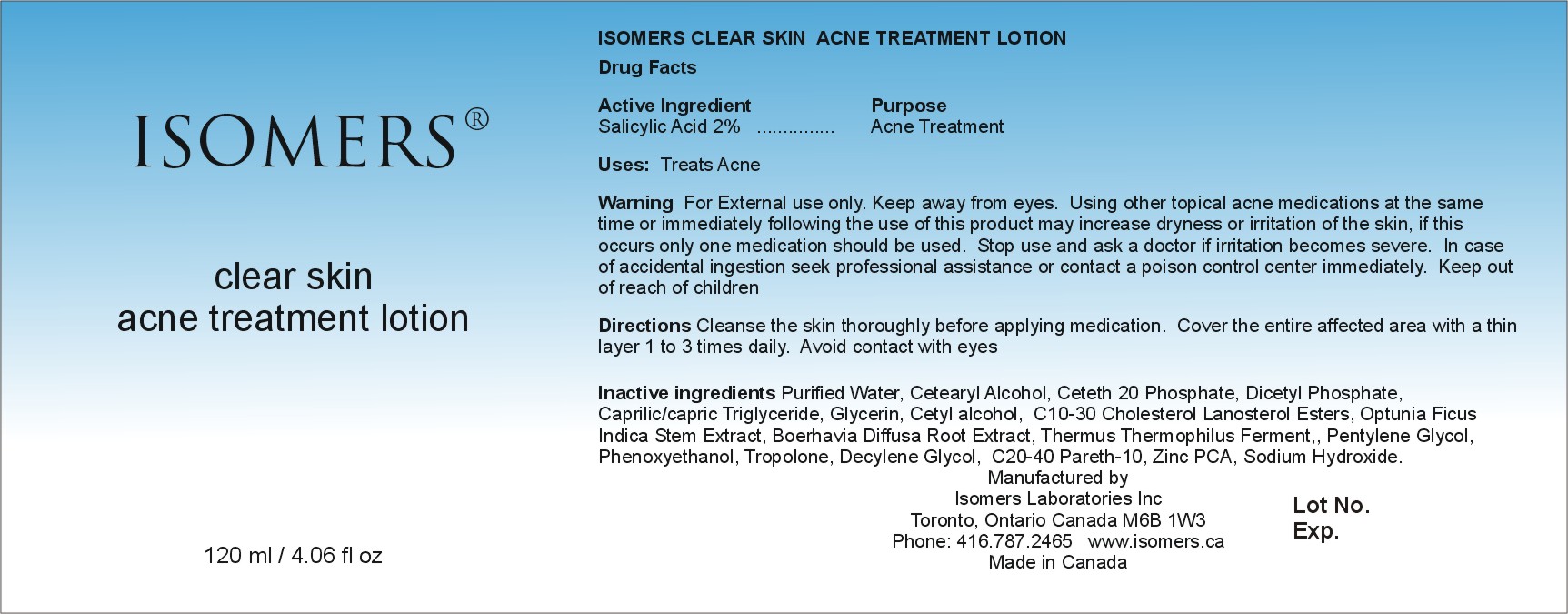 DRUG LABEL: Isomers Clear Skin Acne Treatment Lotion
NDC: 64990-605 | Form: LOTION
Manufacturer: Isomers Laboratories Inc
Category: otc | Type: HUMAN OTC DRUG LABEL
Date: 20100209

ACTIVE INGREDIENTS: SALICYLIC ACID 0.02 mL/1 mL
INACTIVE INGREDIENTS: WATER; CETOSTEARYL ALCOHOL; DIHEXADECYL PHOSPHATE; MEDIUM-CHAIN TRIGLYCERIDES; GLYCERIN; CETYL ALCOHOL; OPUNTIA FICUS-INDICA; PHENOXYETHANOL; SODIUM HYDROXIDE

DRUG FACTS

ACTIVE INGREDIENT

Enter section text here

Active ingredient:

Salicylic Acid 2%

PURPOSE

Enter section text here

Purpose:

Acne Treatment

ASK DOCTOR

Enter section text here

STOP USE AND ASK DOCTOR

If irritation becomes Severe

KEEP OUT OF REACH OF CHILDREN

Enter section text here

Keep out of reach of children

WARNINGS

Enter section text here

Warnings:

- For external use only
- Keep away from eyes
- Using other topical acne medications at the same time or immediately following the use of this product may increase dryness or irritation of the skin, if this occurs only one medication should be used.
- In case of accidental ingestion seek professional assistance or contact a poison control center immediately.

INACTIVE INGREDIENT

Enter section text here

Inactive Ingredients:

Purified Water, Cetearyl Alcohol, Ceteth 20 Phosphate, Dicetyl Phosphate, Caprylic/Capric Triglyceride, Glycerin, Cetyl Alcohol, C 10- 30 Cholesterol Lanosterol Esters, Optunia Ficus Indica Stem extract, Boerhavia Diffusa root extract, Thermus Thermophilus Ferment, Pentylene Glycol, Phenoxyethanol, Tropolone, Decylene Glycol, C 20-40 Pareth-10, Zinc PCA, Sodium Hydroxide.

PACKAGE LABEL

CSATL120.jpg